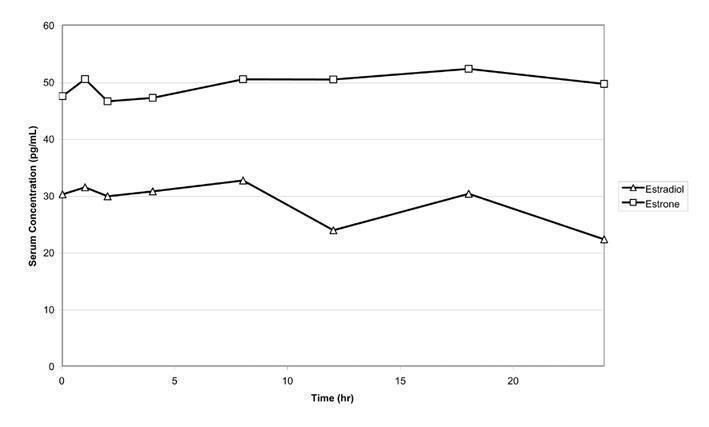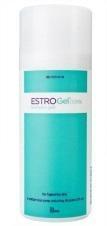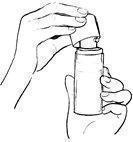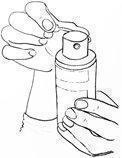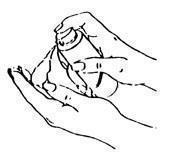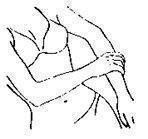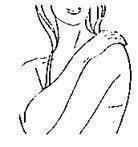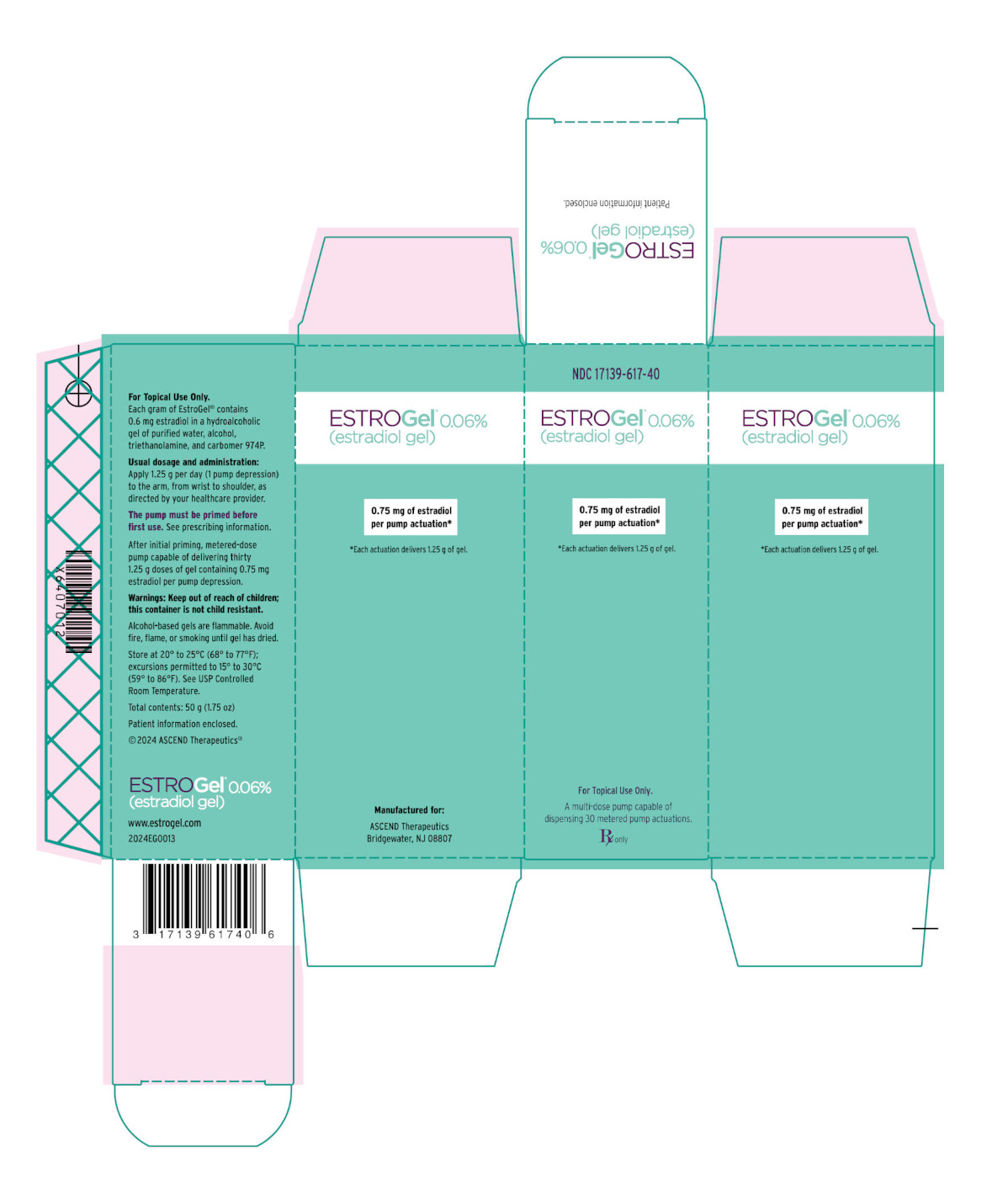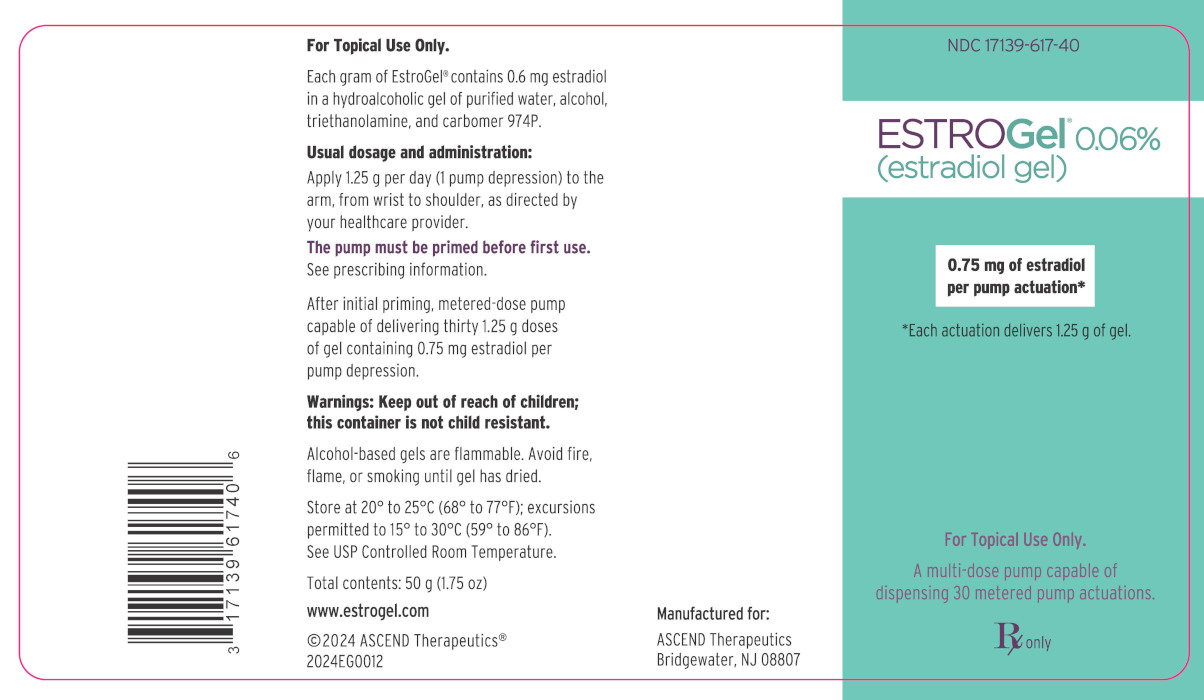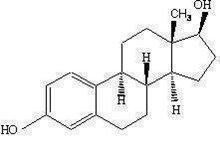 DRUG LABEL: EstroGel
NDC: 17139-617 | Form: GEL, METERED
Manufacturer: ASCEND Therapeutics US, LLC
Category: prescription | Type: HUMAN PRESCRIPTION DRUG LABEL
Date: 20260127

ACTIVE INGREDIENTS: ESTRADIOL 0.75 mg/1.25 g

HIGHLIGHTS OF PRESCRIBING INFORMATION

These highlights do not include all the information needed to use ESTROGEL safely and effectively. See full prescribing information for ESTROGEL.
EstroGel ® 0.06% (estradiol gel) for topical use
Initial U.S. Approval: 1975

WARNING: ENDOMETRIAL CANCER WITH UNOPPOSED ESTROGEN IN WOMEN WITH A UTERUS

See full prescribing information for complete boxed warning

- There is an increased risk of endometrial cancer in women with a uterus who use unopposed estrogens (5.2)

RECENT MAJOR CHANGES

Removed Box Warnings, Cardiovascular disorders | 12/2025
Removed Box Warnings, Breast Cancer | 12/2025
Removed Box Warnings, Probable Dementia | 12/2025
Removed Warnings and Precautions, Probable Dementia (5.3) | 12/2025

1 INDICATIONS AND USAGE

EstroGel 0.06% is an estrogen indicated for:

- Treatment of moderate to severe vasomotor symptoms due to menopause (1.1)
- Treatment of moderate to severe symptoms of vulvar and vaginal atrophy due to menopause (1.2)

2 DOSAGE AND ADMINISTRATION

Metered-dose pump: Daily administration of EstroGel 0.06% 1.25 g per day (1 pump depression) to the arm (2.1, 2.2, 2.3)

3 DOSAGE FORMS AND STRENGTHS

Gel: 1 pump depression of EstroGel 0.06% delivers 1.25 g of gel containing 0.75 mg estradiol (3)

4 CONTRAINDICATIONS

- Undiagnosed abnormal genital bleeding (4, 5.2)
- Breast cancer or a history of breast cancer (4, 5.2)
- Estrogen-dependent neoplasia (4, 5.2)
- Active DVT, PE, or history of these conditions (4, 5.1)
- Active arterial thromboembolic disease (for example, stroke or MI), or a history of these conditions (4, 5.1)
- Known anaphylactic reaction, angioedema, or hypersensitivity to EstroGel (4)
- Hepatic impairment or disease (4, 5.9)
- Protein C, protein S, or antithrombin deficiency, or other known thrombophilic disorders (4)

5 WARNINGS AND PRECAUTIONS

- Estrogens increase the risk of gallbladder disease (5.4)
- Discontinue estrogen if severe hypercalcemia, loss of vision, severe hypertriglyceridemia or cholestatic jaundice occurs (5.5, 5.6, 5.8, 5.9)
- Monitor thyroid function in women on thyroid replacement therapy (5.10)

6 ADVERSE REACTIONS

The most common adverse reactions with EstroGel (≥5 percent) are: headache, flatulence, and breast pain (6.1)

To report SUSPECTED ADVERSE REACTIONS, contact ASCEND Therapeutics® US, LLC at 1-877-204-1013 or FDA at 1-800-FDA-1088 or www.fda.gov/medwatch.

7 DRUG INTERACTIONS

Inducers and/or inhibitors of CYP3A4 may affect estrogen drug metabolism and decrease or increase the estrogen plasma concentration. (7.1)

FULL PRESCRIBING INFORMATION

WARNING: ENDOMETRIAL CANCER WITH UNOPPOSED ESTROGEN IN WOMEN WITH A UTERUS

There is an increased risk of endometrial cancer in a woman with a uterus who uses unopposed estrogens. Adding a progestogen to estrogen therapy has been shown to reduce the risk of endometrial hyperplasia, which may be a precursor to endometrial cancer.

Perform adequate diagnostic measures, including directed or random endometrial sampling when indicated, to rule out malignancy in postmenopausal women with undiagnosed, persistent, or recurring abnormal genital bleeding [see Warnings and Precautions (5.2)].

1 INDICATIONS AND USAGE

1.2 Treatment of Moderate to Severe Symptoms of Vulvar and Vaginal Atrophy due to Menopause.

Limitation of Use
When prescribing solely for the treatment of moderate to severe symptoms of vulvar and vaginal atrophy due to menopause, first consider the use of topical vaginal products.

2 DOSAGE AND ADMINISTRATION

2.1 Important Use Information

The timing of EstroGel initiation can affect the overall benefit-risk profile. Consider initiating EstroGel in women < 60 years old or < 10 years since menopause onset [see Warning and Precautions (5), Use in Specific Populations (8.5) and Clinical Studies (14)].

When estrogen is prescribed for a menopausal woman with a uterus, the addition of a progestogen has been shown to reduce the risk of endometrial cancer. There are possible risks associated with the use of progestogens plus estrogens that differ from those of estrogen-alone regimens. See prescribing information for progestogens indicated for the prevention of endometrial hyperplasia in non-hysterectomized menopausal women receiving estrogens [see Warning and Precautions (5.2, 5.3)].

Generally, a woman without a uterus does not need to use a progestogen with estrogen therapy. In some cases, however, hysterectomized women with a history of endometriosis may benefit from the addition of a progestogen [see Warning and Precautions (5.13)].

2.2 Treatment of Moderate to Severe Vasomotor Symptoms due to Menopause.

EstroGel 0.06% 1.25 g per day is the single approved dose for the treatment of moderate to severe vasomotor symptoms due to menopause.

Before using the canister for the first time, it must be primed. Remove the large canister cover, and fully depress the pump 5 times. Discard the unused gel by thoroughly rinsing down the sink or placing it in the household trash. After priming, the pump is ready to use.

The recommended area of application is the arm. Apply a thin layer over the entire arm on the inside and outside from wrist to shoulder.

2.3 Treatment of Moderate to Severe Symptoms of Vulvar and Vaginal Atrophy due to Menopause.

EstroGel 0.06% 1.25 g per day is the single approved dose for the treatment of moderate to severe symptoms of vulvar and vaginal atrophy due to menopause. The lowest effective dose of EstroGel 0.06% for this indication has not been determined. When prescribing solely for the treatment of moderate to severe symptoms of vulvar and vaginal atrophy, first consider the use of topical vaginal products.

Before using the canister for the first time, it must be primed. Remove the large canister cover, and fully depress the pump 5 times. Discard the unused gel by thoroughly rinsing down the sink or placing it in the household trash. After priming, the pump is ready to use.

The recommended area of application is the arm. Apply a thin layer over the entire arm on the inside and outside from wrist to shoulder.

3 DOSAGE FORMS AND STRENGTHS

EstroGel 0.06% is an estradiol transdermal gel. One pump depression delivers 1.25 g of gel that contains 0.75 mg estradiol.

4 CONTRAINDICATIONS

EstroGel is contraindicated in women with any of the following conditions:

- Abnormal genital bleeding of unknown etiology [see Warning and Precautions (5.2)].
- Current or history of breast cancer [see Warning and Precautions (5.2)].
- Current or history of estrogen-dependent neoplasia [see Warning and Precautions (5.2)].
- Active DVT, PE, or history of these conditions [see Warning and Precautions (5.1)].
- Active arterial thromboembolic disease (for example, stroke or MI), or a history of these conditions [see Warning and Precautions (5.1)].
- Known anaphylactic reaction, angioedema, or hypersensitivity to EstroGel
- Hepatic impairment or disease [see Warning and Precautions (5.9)].
- Protein C, protein S, or antithrombin deficiency, or other known thrombophilic disorders

5 WARNINGS AND PRECAUTIONS

5.1 Cardiovascular Disorders

EstroGel is contraindicated in women with active DVT, PE, stroke, or a history of these conditions [see Contraindications (4)]. Immediately discontinue EstroGel if a PE, DVT, or stroke, occurs or is suspected. If feasible, discontinue EstroGel at least 4 to 6 weeks before surgery of the type associated with an increased risk of thromboembolism, or during periods of prolonged immobilization.

The safety and efficacy of EstroGel for the prevention of cardiovascular disorders have not been established.

The Women’s Health Initiative (WHI) estrogen-alone trial reported increased risks of pulmonary embolism (PE), deep vein thrombosis (DVT), and stroke, in postmenopausal women (50 to 79 years of age, average age 63.4 years) during 7.2 years of treatment with daily oral conjugated estrogens (CE) [0.625 mg] relative to placebo. Analyses were also conducted in women aged 50-59 years, a group of women more likely to present with new onset of moderate to severe VMS compared to women of other age groups in the trial.

Only daily oral 0.625 mg CE was studied in the WHI estrogen-alone trial. Therefore, the relevance of the WHI findings regarding adverse cardiovascular events to lower CE doses, other routes of administration, or other estrogen products is not known. Without such data, it is not possible to definitively exclude these risks or determine the extent of these risks for other products [see Clinical Studies (14.3)].

Venous Thromboembolism
In women aged 50-59 years, the WHI estrogen-alone trial reported a relative risk for PE of 1.53 (95% confidence interval [CI], 0.63, 3.75) for CE compared to placebo, with an absolute risk difference of 4 per 10,000 women-years (WYs; 10 versus 6). The relative risk for DVT was 1.66 (95% CI 0.75, 3.67) for CE compared to placebo, with a risk difference of 5 per 10,000 WYs (13 versus 8).

In the overall study population of women aged 50-79 years, the WHI estrogen-alone trial reported a relative risk of PE of 1.35 (95% CI 0.89, 2.05) for CE compared to placebo, with a risk difference of 4 per 10,000 WYs (14 versus 10). The relative risk for DVT was 1.48 (95% 1.06, 2.07) for CE compared to placebo, with a risk difference of 7 per 10,000 WYs (23 versus 15) [see Clinical Studies (14.3, 14.4)].

Stroke
In women aged 50-59 years, the WHI estrogen-alone trial reported a relative risk for stroke of 0.99 (95% 0.53, 1.85) for CE compared to placebo, with a risk difference of -1 per 10,000 WYs (16 versus 17). ^3

In the overall study population of women aged 50-79 years, the WHI estrogen-alone trial reported a relative risk for stroke of 1.35 (95%, 1.07, 1.70) for CE compared to placebo, with a risk difference of 11 per 10,000 WYs (45 versus 34) [see Clinical Studies (14.3)]. ^3

Coronary Heart Disease
The WHI estrogen-alone sub-study reported no overall effect on coronary heart disease (CHD) events (defined as nonfatal MI, silent MI, or CHD death) in women receiving estrogen-alone compared to placebo^2 [see Clinical Studies (14.4)].

Subgroup analyses of women 50 to 59 years of age, who were less than 10 years since menopause, suggest a reduction (not statistically significant) of CHD events in those women receiving CE (0.625 mg)-alone compared to placebo) (8 versus 16per 10,000 women-years).^11

5.2 Malignant Neoplasms

Endometrial Cancer

In EstroGel-treated menopausal women with a uterus with persistent or recurring abnormal genital bleeding of unknown etiology, perform adequate diagnostic measures, including directed or random endometrial sampling when indicated, to assess for endometrial cancer.

An increased risk of endometrial cancer has been reported with the use of unopposed estrogen therapy in women with a uterus. The reported endometrial cancer risk among unopposed estrogen users is about 2 to 12 times greater than in non-users and appears dependent on duration of treatment and on estrogen dose. Most studies show no significant increased risk associated with the use of estrogens for less than 1 year. The greatest risk appears to be associated with prolonged use, with increased risks of 15- to 24-fold for 5 to 10 years or more. This risk has been shown to persist for at least 8 to 15 years after estrogen therapy is discontinued. There is no evidence that the use of natural estrogens results in a different endometrial risk profile than synthetic estrogens of equivalent estrogen dose.

Adding a progestogen to estrogen-alone therapy has been shown to reduce the risk of endometrial hyperplasia, which may be a precursor to endometrial cancer. There are, however, possible risks associated with the use of progestogens plus estrogens that differ from those of estrogen-alone regimens [see Warnings and Precautions (5.3)].

Breast Cancer

Surveillance measures for breast cancer, such as breast examinations and mammography, are recommended. The use of estrogen-alone therapy has been reported to result in an increase in abnormal mammograms requiring further evaluation.

In the WHI estrogen-alone trial, after an average follow-up of 7.1 years, daily CE-alone was not associated with an increased risk of invasive breast cancer. Among women 50-59 years old, the relative risk was 0.82 (95% CI, 0.50, 1.34) for CE compared to placebo, with a risk difference of -5 per 10,000 WYs (24 versus 29). In the overall study population of women aged 50-79 years (average age 63.4 years), the relative risk was 0.79 (95% CI, 0.61, 1.02), with a risk difference of -7 per 10,000 WYs (28 versus 35). [see Clinical Studies (14.4)]. However, a large meta-analysis including 24 prospective studies of postmenopausal women comparing current use of estrogen-only products with use duration of 5 to 14 years (average of 9 years) versus never use reported a relative risk for breast cancer of 1.33 (95% CI, 1.28 to 1.38).^4

Ovarian Cancer

A large meta-analysis including 17 prospective studies of postmenopausal women compared current use of estrogen-only products versus never use and reported a relative risk for ovarian cancer of 1.37 (95% CI, 1.26 to 1.50). The duration of hormone therapy use that was associated with an increased risk of ovarian cancer is unknown. ^5

5.3 Risks Associated with Concomitant Use of Estrogen Plus Progestogen

If EstroGel is administered with a progestogen, there are possible risks associated with the use of progestogens plus estrogens that differ from those of estrogen-alone regimens. Refer to prescribing information for progestogens indicated for the prevention of endometrial hyperplasia in non-hysterectomized menopausal women receiving estrogens.

5.4 Gallbladder Disease

A 2- to 4-fold increase in the risk of gallbladder disease requiring surgery in postmenopausal women receiving estrogens has been reported.

5.5 Hypercalcemia

Estrogen administration may lead to severe hypercalcemia in women with breast cancer and bone metastases. Discontinue estrogens, including EstroGel if hypercalcemia occurs, and take appropriate measures to reduce the serum calcium level.

5.6 Visual Abnormalities

Retinal vascular thrombosis has been reported in women receiving estrogens. Discontinue EstroGel pending examination if there is sudden partial or complete loss of vision or a sudden onset of proptosis, diplopia, or migraine. Permanently discontinue estrogens, including EstroGel. if examination reveals papilledema or retinal vascular lesions.

5.7 Elevated Blood Pressure

In a small number of case reports, substantial increases in blood pressure have been attributed to idiosyncratic reactions to estrogens. In a large, randomized, placebo-controlled clinical trial, a generalized effect of estrogens on blood pressure was not seen.

5.8 Exacerbation of Hypertriglyceridemia

In women with pre-existing hypertriglyceridemia, estrogen therapy may be associated with elevations of plasma triglycerides leading to pancreatitis. Discontinue EstroGel if pancreatitis occurs.

5.9 Hepatic Impairment and/or Past History of Cholestatic Jaundice

Estrogens may be poorly metabolized in women with hepatic impairment. Exercise caution in any woman with a history of cholestatic jaundice associated with past estrogen use or with pregnancy. In the case of recurrence of cholestatic jaundice, discontinue EstroGel.

5.10 Exacerbation of Hypothyroidism

Estrogen administration leads to increased thyroid-binding globulin (TBG) levels. Women with normal thyroid function can compensate for the increased TBG by making more thyroid hormone, thus maintaining free T4 and T3 serum concentrations in the normal range. Women dependent on thyroid hormone replacement therapy who are also receiving estrogens may require increased doses of their thyroid replacement therapy. Monitor thyroid function in these women during treatment with EstroGel to maintain their free thyroid hormone levels in an acceptable range.

5.11 Fluid Retention

Estrogens may cause some degree of fluid retention. Monitor any woman with a condition(s) that might predispose her to fluid retention, such as cardiac or renal impairment., Discontinue estrogen-alone therapy, including EstroGel, with evidence of medically concerning fluid retention.

5.12 Hypocalcemia

Estrogen-induced hypocalcemia may occur in women with hypoparathyroidism. Consider whether the benefits of estrogen therapy, including EstroGel, outweigh the risks in women.

5.13 Exacerbation of Endometriosis

A few cases of malignant transformation of residual endometrial implants have been reported in women treated post-hysterectomy with estrogen-alone therapy. Consider the addition of progestogen therapy for women known to have residual endometriosis post-hysterectomy.

5.14 Hereditary Angioedema

Exogenous estrogens may exacerbate symptoms of angioedema in women with hereditary angioedema. Consider whether the benefits of estrogen therapy, including EstroGel, outweigh the risks in such women.

5.15 Exacerbation of Other Conditions

Estrogen therapy, including EstroGel, may cause an exacerbation of asthma, diabetes mellitus, epilepsy, migraine, porphyria, systemic lupus erythematosus, and hepatic hemangiomas. Consider whether the benefits of estrogen therapy outweigh the risks in women with such conditions.

5.16 Alcohol-based Products are Flammable

Avoid fire, flame, or smoking until EstroGel has dried.

5.17 Moisturizer Lotion Application

Moisturizer Lotion Application [see Clinical Pharmacology (12.3)].

5.18 Laboratory Tests

Serum follicle stimulating hormone (FSH) and estradiol levels have not been shown to be useful in the management of postmenopausal women with moderate to severe vasomotor symptoms and moderate to severe symptoms of vulvar and vaginal atrophy.

5.19 Drug-Laboratory Test Interactions

- Accelerated prothrombin time, partial thromboplastin time, and platelet aggregation time; increased platelet count; increased factors II, VII antigen, VIII antigen, VIII coagulant activity, IX, X, XII, VII-X complex, II-VII-X complex, and beta‑thromboglobulin; decreased levels of anti-factor Xa and antithrombin III, decreased antithrombin III activity; increased levels of fibrinogen and fibrinogen activity; increased plasminogen antigen and activity.
- Increased thyroid-binding globulin (TBG) levels leading to increased circulating total thyroid hormone levels, as measured by protein-bound iodine (PBI), T4 levels (by column or by radioimmunoassay) or T3 levels by radioimmunoassay. T3 resin uptake is decreased, reflecting the elevated TBG. Free T4 and T3 concentrations are unaltered. Women on thyroid-replacement therapy may require higher doses of thyroid hormone.
- Other binding proteins may be elevated in serum (for example, corticosteroid-binding globulin [CBG], sex hormone-binding globulin [SHBG]), leading to increased total circulating corticosteroids and sex steroids, respectively. Free hormone concentrations, such as testosterone and estradiol, may be decreased. Other plasma proteins may be increased (angiotensinogen/renin substrate, alpha‑1‑antitrypsin, ceruloplasmin).
- Increased plasma high-density lipoprotein (HDL) and HDL2 cholesterol subfraction concentrations, reduced low-density lipoprotein (LDL) cholesterol concentration, increased triglyceride levels.
- Impaired glucose tolerance.

6 ADVERSE REACTIONS

The following serious adverse reactions are discussed elsewhere in the labeling:

- Cardiovascular Disorders [see Boxed Warning, and Warnings and Precautions (5.1)]
- Malignant Neoplasms [see Boxed Warning, and Warnings and Precautions (5.2)]

6.1 Clinical Trials Experience

Because clinical trials are conducted under widely varying conditions, adverse reaction rates observed in the clinical trials of a drug cannot be directly compared to rates in the clinical trials of another drug and may not reflect the rates observed in clinical practice.

EstroGel was studied in 2 well-controlled, 12-week clinical trials. Incidence of adverse drug reactions ≥5 percent for 1.25 g EstroGel 0.06% and placebo is given in Table 1.

Table 1
Incidence of Adverse Drug Reactions ≥5 Percent Occurrence in the EstroGel Treatment Group for the Intent-to-Treat Safety Population in 2 Well-controlled Clinical Studies (Expressed as Percent of Treatment Group)
Body System/ Adverse Drug Reactions | EstroGel 0.06% 1.25 g /day (n=168) | Placebo (n=73)
BODY AS A WHOLE
Headache | 9.5 | 2.7
DIGESTIVE SYSTEM
Flatulence | 5.4 | 4.1
UROGENITAL SYSTEM
Breast pain | 10.7 | 8.2

In 2 controlled clinical trials, application site reactions were reported by 0.6 percent of patients who received 1.25 g of EstroGel. Other skin reactions, such as pruritus and rash, were also noted.

6.2 Postmarketing Experience

The following adverse reactions have been identified during post-approval use of EstroGel. Because these reactions are reported voluntarily from a population of uncertain size, it is not always possible to reliably estimate their frequency or establish a causal relationship to drug exposure.

Genitourinary system

Endometrial cancer Breast Pain; tenderness; breast cancer

Cardiovascular

Deep vein thrombosis; myocardial ischemia; phlebitis

Gastrointestinal

Nausea; abdominal distension; diarrhea; stomach discomfort

Skin

Alopecia; rash; pruritus; application site: dryness, pain, discoloration, reaction, rash

Eyes

Retinal vein occlusion

Central nervous system

Headache; dizziness; insomnia; hypoesthesia; meningioma; aphasia; bradyphrenia; paresthesia

Miscellaneous

Drug ineffective; hot flush; arthralgia; night sweats; drug effect decreased; pain in extremity; fatigue; weight increased; pain; hypersensitivity; dyspnea; malignant mesenchymoma; angioedema; hepatitis acute; face edema; accidental exposure; myoclonus; gait disturbance; flushing

7 DRUG INTERACTIONS

In vitro and in vivo studies have shown that estrogens are metabolized partially by cytochrome P450 3A4 (CYP3A4). Therefore, inducers or inhibitors of CYP3A4 may affect estrogen drug metabolism. Inducers of CYP3A4, such as St. John’s wort (Hypericum perforatum) preparations, phenobarbital, carbamazepine, and rifampin, may reduce plasma concentrations of estrogens, possibly resulting in a decrease in therapeutic effects and/or changes in the uterine bleeding profile. Inhibitors of CYP3A4 such as erythromycin, clarithromycin, ketoconazole, itraconazole, ritonavir, and grapefruit juice may increase plasma concentrations of estrogen and may result in adverse reactions.

8 USE IN SPECIFIC POPULATIONS

8.1 Pregnancy

Risk Summary

EstroGel is not indicated for use in pregnancy . There are no data with the use of EstroGel in pregnant women, however, epidemiologic studies and meta-analysis have not found an increased risk of genital or non-genital birth defects (including cardiac anomalities and limb-reduction defects) following exposure to combined hormonal contraceptives (estrogens and progestins) before conception or during early pregnancy.

In the U.S. general population, the estimated background rate of major birth defects and miscarriage in clinically recognized pregnancies is 2% to 4% and 15% to 20%, respectively.

8.3 Lactation

Estrogens are present in human milk and can reduce milk production in breast-feeding women. This reduction can occur at any time but is less likely to occur once breast-feeding is well established. The development and health benefits of breastfeeding should be considered along with the mother’s clinical need for EstroGel and any potential adverse effects on the breastfed child from EstroGel or from the underlying maternal condition.

8.4 Pediatric Use

EstroGel is not indicated for use in pediatric patients. Clinical studies have not been conducted in the pediatric population.

8.5 Geriatric Use

There have not been sufficient numbers of geriatric women involved in clinical studies utilizing EstroGel to determine whether those over 65 years of age differ from younger subjects in their response to EstroGel.

The Women’s Health Initiative Studies
In the WHI estrogen-alone trial (daily CE [0.625 mg]-alone versus placebo), there was a higher relative risk of stroke in women greater than 65 years of age [see Clinical Studies (14.3, 14.4)].

The Women’s Health Initiative Memory Study
In the WHIMS ancillary studies of postmenopausal women 65 to 79 years of age, there was an increased risk of probable dementia in women receiving estrogen-alone [see Clinical Studies (14.4, 14.5)].

Since the trial was conducted in women 65 to 79 years of age, it is unknown whether these findings apply to younger menopausal women [see Clinical Studies (14.4, 14.5)]. The safety and efficacy of EstroGel for the prevention of dementia has not been established.

10 OVERDOSAGE

Overdosage of estrogen may cause nausea, vomiting, breast tenderness, abdominal pain, drowsiness and fatigue, and withdrawal bleeding may occur in women. Treatment of overdose consists of discontinuation of EstroGel therapy with institution of appropriate symptomatic care.

11 DESCRIPTION

EstroGel (estradiol gel) contains 0.06 percent estradiol in an absorptive hydroalcoholic gel base for topical application. It is a clear, colorless gel, which is odorless when dry. One pump depression of EstroGel delivers 1.25 g of gel containing 0.75 mg estradiol.

Estradiol is a white crystalline powder, chemically described as estra‑1,3,5(10)-triene-3,17β-diol. It has an empirical formula of C18H24O2 and molecular weight of 272.39. The structural formula is:

The active component of the gel is estradiol. The remaining components of the gel (purified water, alcohol, triethanolamine and carbomer 934P) are pharmacologically inactive.

12 CLINICAL PHARMACOLOGY

12.1 Mechanism of Action

Endogenous estrogens are largely responsible for the development and maintenance of the female reproductive system and secondary sexual characteristics. Although circulating estrogens exist in a dynamic equilibrium of metabolic interconversions, estradiol is the principal intracellular human estrogen and is substantially more potent than its metabolites, estrone and estriol, at the receptor level.

The primary source of estrogen in normally cycling adult women is the ovarian follicle, which secretes 70 to 500 mcg of estradiol daily, depending on the phase of the menstrual cycle. After menopause, most endogenous estrogen is produced by conversion of androstenedione, secreted by the adrenal cortex, to estrone in the peripheral tissues. Thus, estrone and the sulfate conjugated form, estrone sulfate, are the most abundant circulating estrogens in postmenopausal women.

Estrogens act through binding to nuclear receptors in estrogen-responsive tissues. To date, 2 estrogen receptors have been identified. These vary in proportion from tissue to tissue.

Circulating estrogens modulate the pituitary secretion of the gonadotropins, luteinizing hormone (LH) and FSH through a negative feedback mechanism. Estrogens act to reduce the elevated levels of these hormones seen in postmenopausal women.

12.2 Pharmacodynamics

Generally, a serum estrogen concentration does not predict an individual woman’s therapeutic response to EstroGel nor her risk for adverse outcomes. Likewise, exposure comparisons across different estrogen products to infer efficacy or safety for the individual woman may not be valid.

12.3 Pharmacokinetics

Absorption

Estradiol is transported across intact skin and into the systemic circulation by a passive diffusion process. The rate of diffusion across the stratum corneum is the rate- limiting factor. When EstroGel is applied to the skin, it dries in 2 to 5 minutes. EstroGel 1.25 g (containing 0.75 mg of estradiol) was administered to 24 postmenopausal women once daily on the posterior surface of 1 arm from wrist to shoulder for 14 consecutive days. Mean maximal serum concentrations of estradiol and estrone on Day 14 were 46.4 pg/mL and 64.2 pg/mL, respectively. The time-averaged serum estradiol and estrone concentrations over the 24-hour dose interval after administration of 1.25 g EstroGel on Day 14 are 28.3 pg/mL and 48.6 pg/mL, respectively. Mean concentration-time profiles for unadjusted estradiol and estrone on Day 14 are shown in Figure 1.

FIGURE 1
Mean Serum Concentration-time Profiles for Unadjusted Estradiol and Estrone After Multiple-dose Applications of 1.25 g EstroGel 0.06% for 14 Days

The serum concentrations of estradiol following 2.5 g EstroGel applications (1.25 g on each arm from wrist to shoulder) appeared to reach steady state after the third daily application.

Distribution

The distribution of exogenous estrogens is similar to that of endogenous estrogens. Estrogens are widely distributed in the body and are generally found in higher concentrations in the sex hormone target organs. Estrogens circulate in blood largely bound to SHBG and albumin.

Metabolism

Exogenous estrogens are metabolized in the same manner as endogenous estrogens. Circulating estrogens exist in a dynamic equilibrium of metabolic interconversions. These transformations take place mainly in the liver. Estradiol is converted reversibly to estrone, and both can be converted to estriol, which is a major urinary metabolite. Estrogens also undergo enterohepatic recirculation via sulfate and glucuronide conjugation in the liver, biliary secretion of conjugates into the intestine, and hydrolysis in the intestine followed by reabsorption. In postmenopausal women, a significant proportion of the circulating estrogens exist as sulfate conjugates, especially estrone sulfate, which serves as a circulating reservoir for the formation of more active estrogens. Although the clinical significance has not been determined, estradiol from EstroGel does not go through first-pass liver metabolism.

Excretion

Estradiol, estrone, and estriol are excreted in the urine along with glucuronide and sulfate conjugates.

The apparent terminal exponential half-life for estradiol was about 36 hours following administration of 1.25 g EstroGel.

Effect of Application Site Washing

The effect of application site washing on the serum concentrations of estradiol was determined in 24 healthy postmenopausal women who applied 1.25 g of EstroGel once daily for 14 consecutive days. Site washing 1 hour after the application resulted in a 22 percent mean decrease in average 24-hour serum concentrations of estradiol.

Potential for Estradiol Transfer

The effect of estradiol transfer was evaluated in 24 healthy postmenopausal women who topically applied 1.25 g of EstroGel once daily on the posterior surface of 1 arm from wrist to shoulder for a period of 14 consecutive days. On each day, 1 hour after gel application, a cohort of 24 non-dosed healthy postmenopausal females directly contacted the dosed cohort at the site of gel application for 15 minutes. No change in endogenous mean serum concentrations of estradiol was observed in the non-dosed cohort after direct skin-to-skin contact with subjects administered EstroGel.

Effect of Moisturizer Lotion/Sunscreen on Estradiol Absorption

The effect of sunscreen and moisturizer lotion on estradiol absorption from 0.06% estradiol topical gel was evaluated in a randomized, open-label, three-period crossover study in 42 healthy postmenopausal women. The study results showed that repeated daily application of sunscreen for 7 days at 1 hour after the administration of 0.06% estradiol topical gel decreased the mean AUC0-24h and Cmax of estradiol by 16%. Repeated daily application of moisturizer lotion for 7 days at 1 hour after the administration of 0.06% estradiol topical gel increased the mean AUC0-24h and Cmax of estradiol by 38% and 73%, respectively.

The effect of daily application of sunscreen/moisturizer lotion on estradiol absorption, when sunscreen/moisturizer lotion is applied before administration of 0.06% estradiol topical gel, was not studied.

13 NONCLINICAL TOXICOLOGY

13.1 Carcinogenesis, Mutagenesis, Impairment of Fertility

Long-term, continuous administration of natural and synthetic estrogens in certain animal species increases the frequency of carcinomas of the breast, uterus, cervix, vagina, testis, and liver.

14 CLINICAL STUDIES

14.1 Effects on Vasomotor Symptoms in Postmenopausal Women

In a placebo-controlled study, 145 postmenopausal women between 29 and 67 years of age (81.4 percent were White) were randomly assigned to receive 1.25 g of EstroGel (containing 0.75 mg of estradiol) or placebo gel for 12 weeks. Efficacy was assessed at 4 and 12 weeks of treatment. A statistically significant reduction in the frequency and severity of moderate to severe hot flushes was shown at Weeks 4 and 12. (See Table 2)

TABLE 2
Mean Change from Baseline in the Number and Severity of Hot Flushes per Day, ITT Population, LOCF
 | Number of Hot Flushes/Day; (Moderate to Severe) |  | Severity Score/Day; (Mild, Moderate, Severe)
 | Placebo; n=73 | EstroGel 0.06%; 1.25 g; n=72 | Placebo; n=73 | EstroGel 0.06%; 1.25 g; n=72
Baseline; Mean (SD) | 11.01 (5.66) | 10.33 (3.07) | 2.30 (0.24) | 2.36 (0.29)
Week 4 [Primary timepoint.]; Mean (SD); Mean change from baseline (SD); Diff. vs placebo; P value [P values from Elteren’s nonparametric test.] | 5.95 (5.17); -5.06 (4.91) | 4.43 (4.13); -5.91 (3.68); 0.85; 0.019 [Statistically significantly different from placebo.] | 2.00 (0.63); -0.31 (0.62) | 1.73 (0.73); -0.63 (0.71); 0.32; 0.005
Week 12; Mean (SD); Mean change from baseline (SD); Diff. vs placebo; P value | 5.17 (6.52); -5.84 (4.52) | 2.79 (3.70); -7.55 (3.52); 1.71; 0.043 | 1.76 (0.84); -0.54 (0.84) | 1.33 (0.97); -1.03 (0.94); 0.49; <0.001

14.2 Effects on Vulvar and Vaginal Atrophy in Postmenopausal Women

Results of the vaginal wall cytology showed a significant (P0.001) increase from baseline in the percent of superficial epithelial cells at Week 12 for 1.25 g EstroGel. In contrast, no significant change from baseline was observed in the placebo group.

14.3 Women’s Health Initiative Studies

The WHI enrolled approximately 27,000 predominantly healthy postmenopausal women in two substudies to assess the risks and benefits of daily oral CE (0.625 mg)-alone or in combination with MPA (2.5 mg) compared to placebo in the prevention of certain chronic diseases. The primary endpoint was the incidence of CHD (defined as nonfatal MI, silent MI, and CHD death), with invasive breast cancer as the primary adverse outcome. A “global index” included the earliest occurrence of CHD, invasive breast cancer, stroke, PE, endometrial cancer (only in the CE plus MPA substudy), colorectal cancer, hip fracture, or death due to other causes. These substudies did not evaluate the effects of CE-alone or CE plus MPA on menopausal symptoms.

WHI Estrogen-Alone Substudy
The WHI estrogen-alone substudy was stopped early because an increased risk of stroke was observed, and it was deemed that no further information would be obtained regarding the risks and benefits of estrogen-alone in predetermined primary endpoints. Results of the estrogen-alone substudy, which included 10,739 women (average 63 years of age, range 50-79; 75.3 percent White, 15.1 percent Black, 6.1 percent Hispanic, 3.6 percent Other), after an average follow-up of 7.1 years are presented in Table 3.

TABLE 3
Relative and Absolute Risk Seen in the Estrogen-Alone Substudy of WHIa
Event | Relative Risk CE vs. Placebo (95% nCIb) | CE; n = 5,310 | Placebo; n = 5,429
 |  | Absolute Risk per 10,000; Women-Years
CHD eventsc | 0.95 (0.78-1.16) | 54 | 57
Non-fatal MIc | 0.91 (0.73-1.14) | 40 | 43
CHD deathc | 1.01 (0.71-1.43) | 16 | 16
All strokesc; Ischemic strokec | 1.33 (1.05-1.68); 1.55 (1.19-2.01) | 45; 38 | 33; 25
Deep vein thrombosisc,d | 1.47 (1.06-2.06) | 23 | 15
Pulmonary embolismc | 1.37 (0.90-2.07) | 14 | 10
Invasive breast cancerc | 0.80 (0.62-1.04) | 28 | 34
Colorectal cancerc | 1.08 (0.75-1.55) | 17 | 16
Hip fracturec | 0.65 (0.45-0.94) | 12 | 19
Vertebral fracturesc,d | 0.64 (0.44-0.93) | 11 | 18
Lower arm/wrist fracturesc,d | 0.58 (0.47-0.72) | 35 | 59
Total fracturesc,d | 0.71 (0.64-0.80) | 144 | 197
Death due to other causese,f | 1.08 (0.88-1.32) | 53 | 50
Overall mortalityc,d | 1.04 (0.88-1.22) | 79 | 75
Global indexg | 1.02 (0.92-1.13) | 206 | 201
a Adapted from numerous WHI publications. WHI publications can be viewed at www.nhlbi.nih.gov/whi.
b Nominal confidence intervals unadjusted for multiple looks and multiple comparisons.
c Results are based on centrally adjudicated data for an average follow-up of 7.1 years.
d Not included in “global index”.
e Results are based on an average follow-up of 6.8 years.
f All deaths, except from breast or colorectal cancer, definite or probable CHD, PE or cerebrovascular disease.
g A subset of the events was combined in a "global index," defined as the earliest occurrence of CHD events, invasive breast cancer, stroke, pulmonary embolism, endometrial cancer, colorectal cancer, hip fracture, or death due to other causes.

For those outcomes included in the WHI “global index” that reached statistical significance, the absolute excess risk per 10,000 women-years in the group treated with CE-alone was 12 more strokes, while the absolute risk reduction per 10,000 women‑years was 7 fewer hip fractures. ^1 The absolute excess risk of events included in the "global index" was a non-significant 5 events per 10,000 women-years. There was no difference between the groups in terms of all-cause mortality .

No overall difference for primary CHD events (nonfatal MI, silent MI, and CHD death) and invasive breast cancer in women receiving CE-alone compared with placebo was reported in final centrally adjudicated results from the estrogen-alone substudy, after an average follow-up of 7.1 years. [See Table 3].

Centrally adjudicated results for stroke events from the estrogen-alone substudy, after an average follow-up of 7.1 years, reported no significant difference in the distribution of stroke subtype or severity, including fatal strokes, in women receiving CE-alone compared to placebo. Estrogen-alone therapy increased the risk of ischemic stroke, and this excess risk was present in all subgroups of women examined.^2

Timing of initiation of estrogen-alone therapy relative to the start of menopause may affect the overall risk benefit profile. The WHI estrogen-alone substudy stratified by age showed in women 50 to 59 years of age a non-significant trend toward reduced risk for CHD [hazard ratio (HR) 0.63 (95 percent CI, 0.36-1.09)] and overall mortality [HR 0.71 (95 percent CI, 0.46-1.11)].

Timing of initiation of estrogen plus progestin therapy relative to the start of menopause may affect the overall risk benefit profile. The WHI estrogen plus progestin substudy stratified by age showed in women 50 to 59 years of age a non-significant trend toward reduced risk for overall mortality [HR 0.69 (95 percent CI, 0.44- 1.07)].

14.4 Women’s Health Initiative Estrogen-Alone Trial

The WHI estrogen-alone trial enrolled predominantly healthy postmenopausal women in trial to assess the risks and benefits of daily oral CE (0.625 mg)- alone compared to placebo in the prevention of certain chronic diseases. The primary endpoint was the incidence of CHD (defined as nonfatal MI, silent MI and CHD death), with invasive breast cancer as the primary adverse outcome. A “global index” included the earliest occurrence of CHD, invasive breast cancer, stroke, PE, colorectal cancer, hip fracture, or death due to other cause. This trial did not evaluate the effects of CE-alone on menopausal symptoms.

The WHI estrogen-alone trial was stopped early because an increased risk of stroke was observed, and it was deemed that no further information would be obtained regarding the risks and benefits of estrogen-alone in predetermined primary endpoints. Centrally adjudicated results for stroke events, after an average follow- up of 7.1 years, reported estrogen-alone increased the risk for ischemic stroke compared to placebo, and this excess risk was present in all subgroups of women examined.

No overall difference for primary CHD events (nonfatal MI, silent MI and CHD death) and invasive breast cancer incidence in women receiving CE-alone compared to placebo was reported in final centrally adjudicated results from the estrogen-alone trial, after an average follow-up of 7.1 years. ^(3, 6,3)

Results of the estrogen-alone trial, which included 10,739 women (average age of 63 years, range 50 to 79 years; 75.3% White, 15.1% Black, 6.1% Hispanic, 3.6% Other), after an average follow- up of 7.1 years are presented in Table A.

Table A: Relative Risk and Risk Difference Observed in the WHI Estrogen-Alone Trial
at an Average of 7.1 Years of Follow-upa
Event | Relative Ratio (95% CI) | Risk Difference (CE vs placebo/10,000 WYs)
CHD events Non-fatal MI CHD death | 0.94 (0.78-1.14) 0.97 (0.79-1.21) 1.00 (0.77-1.31) | -3 (55 vs 58) -1 (44 vs 45) 0 (29 vs 29)
All Strokes | 1.35 (1.07-1.70) | 11 (45 vs 34)
Deep vein thrombosisd | 1.48 (1.06-2.07) | 7 (23 vs 15)
Pulmonary embolism | 1.35 (0.89-2.05) | 4 (14 vs 10)
Invasive breast cancere | 0.79 (0.61-1.02) | -7 (28 vs 35)
Colorectal cancer | 1.15 (0.81-1.64) | 2 (17 vs 15)
Hip fracture | 0.67 (0.46-0.96) | -6 (13 vs 19)
Vertebral fracturesd | 0.64 (0.44-0.93) | -6 (12 vs 18)
Total fracturesd | 0.72 (0.64-0.80) | -61 (153 vs 214)
Overall mortality c,f | 1.03 (0.88-1.21) | 3 (80 vs 77)
Global Indexg | 1.03 (0.93-1.13) | 4 (208 vs 204)
a Adapted from 2013 WHI trial (CE n=5,310, placebo n=5,429). WHI publications can be viewed at www.nhlbi.nih.gov/whi.
b Results are based on centrally adjudicated data.
c In the WHI studies, hazard ratios were estimated using Cox proportional hazards models comparing treatment to placebo; however, they are described here as relative risks. Nominal confidence intervals unadjusted for multiple looks and multiple comparisons.
d Not included in “global index.”
e Includes metastatic and non-metastatic breast cancer with the exception of in situ cancer.
f All deaths, except from breast or colorectal cancer, definite or probable CHD, PE or cerebrovascular disease.
g A subset of the events was combined in a “global index,” defined as the earliest occurrence of CHD events, invasive breast cancer, stroke, PE, colorectal cancer, hip fracture, or death due to other causes.

Timing of the initiation of estrogen-alone therapy relative to the start of menopause may affect the overall risk benefit profile. The study results for women 50-59 years old in the WHI estrogen-alone trial are shown in Table B.

Table B. Relative Risk and Risk Difference Observed Among Women 50-59 Years of Age
in the WHI Estrogen-Alone Trial at an Average of 7.1 Years a,b
Event | Relative Ratio (95% CI)c | Risk Difference (CE vs placebo/10,000 WYs)
CHD events | 0.60 (0.35-1.04) | -11 (17 vs 28)
Non-fatal MI | 0.55 (0.31-1.00) | -11 (14 vs 25)
CHD death | 0.80 (0.32-2.04) | -1 (7 vs 8)
All Strokes | 0.99 (0.53-1.85) | -1 (16 vs 17)
Deep vein thrombosisd | 1.66 (0.75-3.67) | 5 (13 vs 8)
Pulmonary embolism | 1.53 (0.63-3.75) | 4 (10 vs 6)
Invasive breast cancere | 0.82 (0.50-1.34) | -5 (24 vs 29)
Colorectal cancer | 0.71 (0.30-1.67) | -3 (7 vs 10)
Hip fracture | 5.01 (0.59-42.91) | 3 (1 vs 3)
Vertebral fracturesd | 0.50 (0.17-1.47) | -4 (4 vs 8)
Total fracturesd | 0.90 (0.72-1.11) | -16 (133 vs 149)
Overall mortality c,f | 0.70 (0.46-1.09) | -11 (29 vs 40)
Global Indexg | 0.84 (0.66-1.07) | -19 (98 vs 117)
a Adapted from 2013 WHI trial (CE n=1,639; placebo=1,674). WHI publications can be viewed at www.nhlbi.nih.gov/whi
b Results are based on centrally adjudicated data.
c In the WHI studies, hazard ratios were estimated using Cox proportional hazards models comparing treatment to placebo; however, they are described here as relative risks. Nominal confidence intervals unadjusted for multiple looks and multiple comparisons.
d Not included in “global index.”
e Includes metastatic and non-metastatic breast cancer with the exception of in situ cancer.
f All deaths, except from breast or colorectal cancer, definite or probable CHD, PE or cerebrovascular disease.
g A subset of the events was combined in a “global index,” defined as the earliest occurrence of CHD events, invasive breast cancer, stroke, PE, colorectal cancer, hip fracture, or death due to other causes.

14.5 Women's Health Initiative Memory Study

The WHIMS estrogen-alone ancillary study of WHI enrolled 2,947 predominantly healthy hysterectomized postmenopausal women 65 to 79 years of age (45% were 65 to 69 years of age, 36% were 70 to 74 years of age, and 19% were 75 years of age and older) to evaluate the effects of daily CE (0.625 mg)-alone on the incidence of probable dementia (primary outcome) compared to placebo. Probable dementia as defined in this study included Alzheimer’s disease (AD), vascular dementia (VaD) and mixed type (having features of both AD and VaD). The most common classification of probable dementia in the treatment group and the placebo group was AD.

After an average follow-up of 5.2 years, the relative risk of probable dementia for CE a-lone versus placebo was 1.49 (95% CI, 0.83-2.66). The absolute risk of probable dementia for CE-alone versus placebo was 37 versus 25 cases per 10,000 women years. Since the ancillary study was conducted in women 65 to 79 years of age, it is unknown whether these findings apply to younger postmenopausal women [Warnings and Precautions (5.3) and Use in Specific Populations (8.5)].^7

15 REFERENCES

1. Rossouw JE, et al. Postmenopausal Hormone Therapy and Risk of Cardiovascular Disease by Age and Years Since Menopause. JAMA. 2007;297:1465-1477.
2. Hsia J, et al. Conjugated Equine Estrogens and Coronary Heart Disease. Arch Int Med. 2006;166:357-365.
3. Curb JD, et al. Venous Thrombosis and Conjugated Equine Estrogen in Women Without a Uterus. Arch Int Med. 2006;166:772-780.
4. Cushman M, et al. Estrogen Plus Progestin and Risk of Venous Thrombosis. JAMA. 2004;292:1573-1580.
5. Stefanick ML, et al. Effects of Conjugated Equine Estrogens on Breast Cancer and Mammography Screening in Postmenopausal Women With Hysterectomy. JAMA. 2006;295:1647-1657.
6. Chlebowski RT, et al. Influence of Estrogen Plus Progestin on Breast Cancer and Mammography in Healthy Postmenopausal Women. JAMA. 2003;289:3234-3253.
7. Anderson GL, et al. Effects of Estrogen Plus Progestin on Gynecologic Cancers and Associated Diagnostic Procedures. JAMA. 2003;290:1739-1748.
8. Shumaker SA, et al. Conjugated Equine Estrogens and Incidence of Probable Dementia and Mild Cognitive Impairment in Postmenopausal Women. JAMA. 2004;291:2947-2958.
9. Jackson RD, et al. Effects of Conjugated Equine Estrogen on Risk of Fractures and BMD in Postmenopausal Women With Hysterectomy: Results From the Women's Health Initiative Randomized Trial. J Bone Miner Res. 2006;21:817-828.
10. Hendrix SL, et al. Effects of Conjugated Equine Estrogen on Stroke in the Women's Health Initiative. Circulation. 2006;113:2425-2434.

16 HOW SUPPLIED/STORAGE AND HANDLING

16.1 How Supplied

EstroGel is a clear, colorless, hydroalcoholic 0.06 percent estradiol gel supplied in a non aerosol, metered-dose pump. The pump consists of an LDPE inner liner encased in rigid plastic with a resealable polypropylene cap. EstroGel is available in a 50-gram (1.75 oz) size. Each individually packaged 50-gram pump contains 50 grams of gel and can deliver 30 metered 1.25-g doses.

NDC: 17139-617-40............................. (50-gram pump)

16.2 Storage and Handling

Keep out of reach of children.
Store at 20° to 25°C (68° to 77°F); excursions permitted to 15° to 30°C (59° to 86°F) [See USP Controlled Room Temperature].

17 PATIENT COUNSELING INFORMATION

Advise women to read the FDA-approved patient labeling (Patient Information and Instructions for Use)

Vaginal Bleeding

Inform postmenopausal women to report any vaginal bleeding to their healthcare provider as soon as possible [see Warnings and Precautions (5.2)].

Possible Serious Adverse Reactions with Estrogen-Alone Therapy

Inform postmenopausal women of the possible serious adverse reactions of estrogen-alone therapy including Cardiovascular Disorders and Malignant Neoplasms [see Warnings and Precautions (5.1, 5.2).

Possible Common Adverse Reactions with Estrogen-Alone Therapy

Inform postmenopausal women of possible less serious but common adverse reactions of estrogen-alone therapy such as headache, breast pain and tenderness, nausea, and vomiting.

Manufactured for:
ASCEND Therapeutics® US, LLC
Bridgewater, NJ 08807

141399Rev122025
Utilizes EHG® Technology
©2025 ASCEND Therapeutics® US, LLC

Patient Information

EstroGel ® 0.06% (ĕs’ trə jĕl)

(estradiol gel)

Read this Patient Information before you start using EstroGel, and each time you get a refill. There may be new information. This information does not take the place of talking to your healthcare provider about your menopausal symptoms or your treatment.

What is the most important information I should know about EstroGel (an estrogen hormone)?

- Using estrogen-alone may increase your chance of getting cancer of the uterus (womb). Report any unusual vaginal bleeding right away while you are using EstroGel. Vaginal bleeding after menopause may be a warning sign of cancer of the uterus (womb). Your healthcare provider should check any unusual vaginal bleeding to find out the cause.

What is EstroGel?

EstroGel is a prescription medicine gel that contains estradiol (an estrogen hormone).

What is EstroGel used for?

EstroGel is used after menopause to:

- Reduce moderate to severe hot flashes
  Estrogens are hormones made by a woman’s ovaries. The ovaries normally stop making estrogens when a woman is between 45 and 55 years old. This drop in body estrogen levels causes the “change of life” or menopause (the end of monthly menstrual periods). Sometimes, both ovaries are removed during an operation before natural menopause takes place. The sudden drop in estrogen levels causes “surgical menopause.”
  When the estrogen levels begin dropping, some women develop very uncomfortable symptoms, such as feelings of warmth in the face, neck, and chest, or sudden intense feelings of heat and sweating (“hot flashes” or “hot flushes”). In some women, the symptoms are mild, and they will not need to use estrogens. In other women, symptoms can be more severe.

- Treat moderate to severe menopausal changes in and around the vagina
  You and your healthcare provider should talk regularly about whether you still need treatment with EstroGel to control these problems. If you use EstroGel only to treat your menopausal changes in and around your vagina, talk with your healthcare provider about whether a topical vaginal product would be better for you.

Who should not use EstroGel?

Do not start using EstroGel if you:

- have unusual vaginal bleeding
  Vaginal bleeding after menopause may be a warning sign of cancer of the uterus (womb). Your healthcare provider should check any unusual vaginal bleeding to find out the cause.
- have been diagnosed with a bleeding disorder
- currently have or have had certain cancers
  Estrogen may increase the chance of getting certain types of cancer, including cancer of the breast or uterus. If you have or have had cancer, talk with your healthcare provider about whether you should use EstroGel.
- had a stroke or heart attack
- currently have or have had blood clots
- currently have or have had liver problems
- are allergic to EstroGel or any of its ingredients
  See the list of ingredients in EstroGel at the end of this leaflet.

Before you use EstroGel, tell your healthcare provider about all of your medical conditions, including if you:

- have any unusual vaginal bleeding
  Vaginal bleeding after menopause may be a warning sign of cancer of the uterus (womb). Your healthcare provider should check any unusual vaginal bleeding to find out the cause.
- have any other medical conditions that may become worse while you are using EstroGel
  Your healthcare provider may need to check you more carefully if you have certain conditions, such as asthma (wheezing), epilepsy (seizures), diabetes, migraine, endometriosis, lupus, angioedema (swelling of face and tongue), problems with your heart, liver, thyroid, kidneys, or high calcium levels in your blood.
- are going to have surgery or will be on bed rest
  Your healthcare provider will let you know if you need to stop using EstroGel.
- are pregnant or think you may be pregnant
  EstroGel is not for pregnant women.
- are breastfeeding
  The hormone in EstroGel can pass into your breast milk.

Tell your healthcare provider about all the medicines you take, including prescription and over-the-counter medicines, vitamins, and herbal supplements. Some medicines may affect how EstroGel works. EstroGel may also affect how your other medicines work. Keep a list of your medicines and show it to your healthcare provider and pharmacist when you get a new medicine.

How should I use EstroGel?

For detailed instructions, see the step-by-step instructions for using EstroGel at the end of this Patient Information.

- Use EstroGel exactly as your healthcare provider tells you to use it.
- EstroGel is for skin use only.
- EstroGel contains alcohol, which is flammable. Avoid fire, flame or smoking until EstroGel has dried.
- You and your healthcare provider should talk regularly (for example, every 3 to 6 months) about the dose you are using and whether you still need treatment with EstroGel.

What are the possible side effects of EstroGel?

Side effects are grouped by how serious they are and how often they happen when you are treated.

Serious, but less common side effects include:

- cancer of the lining of the uterus (womb)
- cancer of the ovary
- high or low blood calcium
- gallbladder disease
- visual abnormalities
- high blood pressure
- high levels of fat (triglycerides) in your blood
- liver problems
- changes in your thyroid hormone levels
- fluid retention
- cancer changes of endometriosis
- enlargement of benign tumors of the uterus (“fibroids”)
- worsening of swelling of face and tongue (angioedema) in women with a history of angioedema
- changes in laboratory test results such as bleeding time and high blood sugar

Call your healthcare provider right away if you get any of the following warning signs or any other unusual symptoms that concern you:

- new breast lumps
- unusual vaginal bleeding
- changes in vision or speech
- sudden new severe headaches
- severe pains in your chest or legs with or without shortness of breath, weakness and fatigue
- swelling of face, lips, and tongue with or without red, itchy bumps

Common side effects of EstroGel include:

- headache
- breast tenderness or pain
- stomach or abdominal cramps, bloating
- nausea and vomiting
- hair loss
- fluid retention
- vaginal yeast infection

These are not all of the possible side effects of EstroGel. For more information, ask your healthcare provider or pharmacist. Tell your healthcare provider if you have any side effects that bother you or do not go away. You may report side effects to FDA at 1-800-FDA-1088 or to ASCEND Therapeutics® US, LLC at 1‑877-204-1013.

What can I do to lower my chances of a serious side effect with EstroGel?

- Talk with your healthcare provider regularly about whether you should continue using EstroGel.
- If you have a uterus, talk with your healthcare provider about whether the addition of a progestogen is right for you.
- In general, the addition of a progestogen is recommended for women with a uterus to reduce the chance of getting cancer of the uterus (womb).
- See your healthcare provider right away if you get vaginal bleeding while using EstroGel.
- Have a pelvic exam, breast exam and mammogram (breast x-ray) every year unless your healthcare provider tells you something else.
- If members of your family have had breast cancer or if you have ever had breast lumps or an abnormal mammogram (breast x-ray), you may need to have breast exams more often.
- If you have high blood pressure, high cholesterol (fat in the blood), diabetes, are overweight, or if you use tobacco, you may have higher chances of getting heart disease.

Ask your healthcare provider for ways to lower your chances of getting heart disease.

How should I store EstroGel?

- Store EstroGel at room temperature between 68°F to 77°F (20°C to 25°C).

Keep EstroGel and all medicines out of the reach of children.

General information about the safe and effective use of EstroGel

Medicines are sometimes prescribed for conditions that are not mentioned in Patient Information leaflets. Do not use EstroGel for conditions for which it was not prescribed. Do not give EstroGel to other people, even if they have the same symptoms you have. It may harm them.
You can ask your healthcare provider or pharmacist for information about EstroGel that is written for health professionals.
For more information, go to www.estrogel.com, or call ASCEND Therapeutics ® US, LLC at 1-877-204-1013.

What are the ingredients in EstroGel?

Active ingredient: estradiol

Inactive ingredients: purified water, alcohol, triethanolamine, and carbomer 974P.

Instructions for Use

EstroGel ® 0.06% (ĕs’ trə jĕl)

(estradiol gel)

Read this Instructions for Use before you start using EstroGel and each time you get a refill. There may be new information. This information does not take the place of talking to your healthcare provider about your menopausal symptoms or your treatment.

You will need the following supplies to use EstroGel: See Figure A.

Figure A

EstroGel is supplied in a metered-dose pump that delivers a measured amount of estradiol to your skin each time you press the pump.
EstroGel is available in a 50-gram canister.

Step 1. Priming the EstroGel pump

- Before using the EstroGel pump for the first time, the pump must be primed. The EstroGel canister contains enough medicine to allow you to prime the pump before you use it for the first time.
- Remove the large cap from the canister. See Figure B.

Figure B

- Slowly push the pump all the way down 5 times. Do not use any EstroGel that came out while priming. Wash it down the sink to avoid accidental exposure to others.
- After priming, the EstroGel pump is ready to use. One complete press of the pump will give the same amount of EstroGel each time.

Step 2. Applying EstroGel to your skin

- Do not allow other people to apply EstroGel to your skin for you.
- Apply EstroGel to clean, dry, unbroken skin.
- Apply EstroGel after your bath or shower. If you go swimming, try to leave as much time as possible between using your EstroGel and going swimming.
- Remove the small cover on the tip of the pump if you have not done so already. See Figure C.

Figure C

- To use EstroGel, press the EstroGel pump firmly and fully 1 time into the palm of your hand. See Figure D.

Figure D

- Using your hand, apply EstroGel to the skin of your other arm. See Figure E.
  Spread the gel as thinly as possible over the entire area on the inside and outside of your arm from your wrist to your shoulder. See Figure F.

Figure E

Figure F

- Do not apply EstroGel directly to your breasts or in and around your vagina.
- Do not massage or rub in EstroGel. Allow the gel to dry for 5 minutes before you get dressed.

Step 3. After you use EstroGel

- Place the small cap back on the tip of the pump. Place the large cap over the top of the canister.
- Wash your hands right away with soap and water after applying EstroGel. This will lower the chance that the medicine will spread from your hands to other people.
- Do not allow others to make contact with the area of skin where you applied the gel for at least 1 hour after application.
- EstroGel is flammable until dry. Let EstroGel dry before smoking or going near an open flame.

Step 4. Throwing away used EstroGel canisters

- The EstroGel 50-gram canister contains enough medicine to allow for priming your canister with up to 5 full pump depressions and delivery of 30 daily doses. After you have first primed your canister and used 30 doses, you will need to throw away the canister. Do not use the canister for more than 30 doses even though the canister may not be completely empty. You may not get the correct dose.

This Patient Information and Instructions for Use has been approved by the U.S. Food and Drug Administration.
Manufactured for:
ASCEND Therapeutics® US, LLC
Bridgewater, NJ 08807
141339Rev122025
Utilizes EHG® Technology
©2025 ASCEND Therapeutics® US, LLC
Revised: 12/2025

PRINCIPAL DISPLAY PANEL - EstroGel 50g

NDC 17139-617-40
ESTROGel® 0.06%
(estradiol gel)
0.75 mg of estradiol
per pump actuation*
*Each actuation delivers 1.25 g of gel
For Topical Use Only.
A multi-dose pump capable of
dispensing 30 metered pump actuations.
Rx only